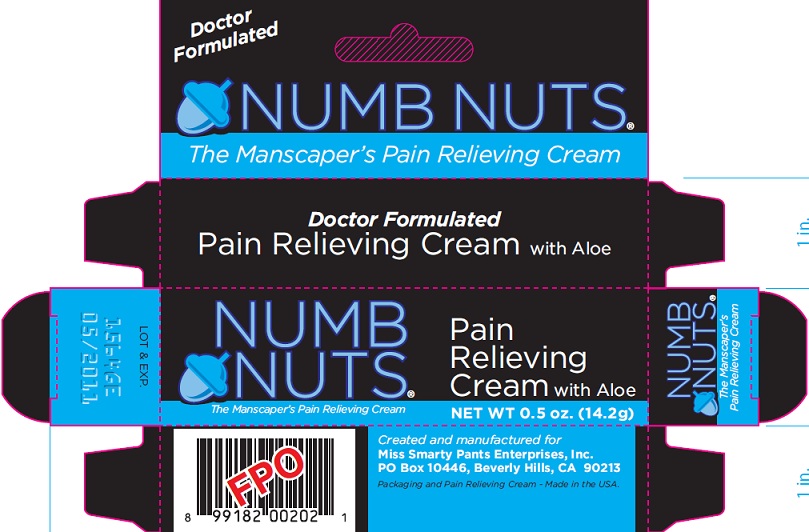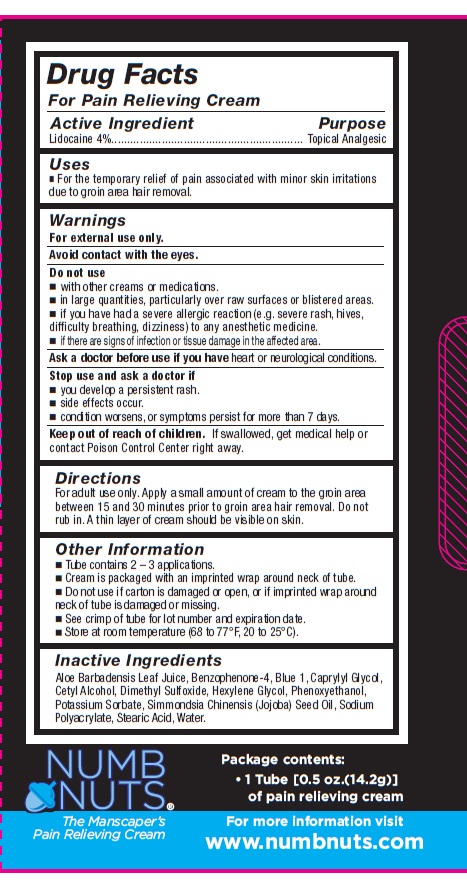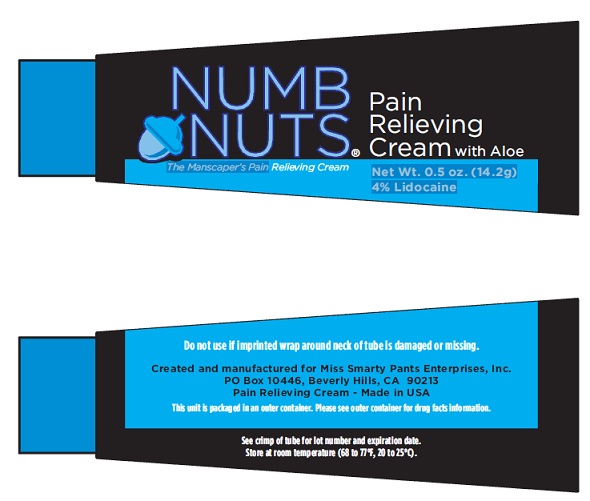 DRUG LABEL: Numb Nuts
NDC: 48095-390 | Form: CREAM
Manufacturer: Miss Smarty Pants Enterprises, Inc.
Category: otc | Type: HUMAN OTC DRUG LABEL
Date: 20100823

ACTIVE INGREDIENTS: LIDOCAINE 4 g/100 g
INACTIVE INGREDIENTS: ALOE VERA FLOWER; CAPRYLYL GLYCOL; CETYL ALCOHOL; HEXYLENE GLYCOL; PHENOXYETHANOL; POTASSIUM SORBATE; JOJOBA OIL; STEARIC ACID; WATER; SULISOBENZONE; DIMETHYL SULFOXIDE

Numb Nuts The Manscaper's Pain Relieving Cream

DRUG FACTS

For Pain Relieving Cream

Active Ingredient Purpose

Lidocaine 4% Topical Analgesic

purpose
topical analgesic

Uses

for the temporary relief of pain associated with minor skin irritations due to groin area hair removal.

WARNINGS

For external use only.

Avoid contact with the eyes

Do not use

with other creams or medications

in large quantities, particularly over raw surfaces or blistered areas

if you have had a severe allergic reaction (e.g. severe rash, hives, difficulty breathing, dizziness) to any anesthetic medicine

if there are signs of infection or tissue damage in the affected area.

Ask a doctor before use if you have heart or neurological conditions.

Stop use and ask a doctor if

you develop a persistent rash

side effects occur

condition worsens or symptoms persist for more than 7 days.

Keep out of reach of children. If swallowed get medical help or contact poison control center right away.

Directions

For adult use only. Apply a small amount of cream to the groin area between 15 and 30 minutes prior to groin area hair removal. Do not rub in. A thin layer of cream should be visible on the skin.

Other information

Cream is packaged with an imprinted wrap around neck of tube

do not use if carton is damaged or open, or if imprinted wrap around neck of tube is damaged or missing.

See crimp of tube for lot number and expiration date

Store at room temperature (68 to 77 degrees F, 20 to 25 degrees C)

INACTIVE INGREDIENT

Aloe Barbadensis Leaf Juice, Caprylyl Glycol, Cetyl Alcohol, Hexylene Glycol, Phenoxyethanol, Potassium Sorbate, Simmondsia Chinesis (Jojoba) Seed Oil, Sodium Polyacrylate, Stearic Acid, Water

Numb Nuts

The Manscaper's Pain Relieving Cream

Pakage contents:

1 Tube [0.5 oz (14.2 g)] of pain relieving cream

for more information visit

www.numbnuts.com

PACKAGE LABEL

NUMB NUTS

The Manscapers Pain Relieving Cream

Doctor Formulated

Pain Relieving Cream with Aloe

NUMB NUTS Pin Relieving Cream with Aloe

The Manscaper's Pain Relieving Cream

Net Wt 0.5 oz (14.2 g)

Created and manufactured for

Miss Smarty Pants Enterprises, Inc.

PO Box 10446, Beverly Hills, CA 90213

Packaging and Pain Relieving Cream-Made in the USA

PACKAGE LABEL

Numb Nuts Pain Relieving Cream with aloe

The manscapers pain relieving cream

Net Wt 0.5 oz (14.2g)

4% Lidocaine

Do Not Use if imprinted wrap around neck of tube is damaged or missing.

Created and manufactured for Miss Smarty Pants Enterprises, Inc.

PO Box 10446 Beverly Hills, CA 90213

Pain Relieving Cream-Made in USA

This unit is packaged in an outer container. Please see outer container for drug facts information.

See crimp of tube for lot number and expiration date.

Store at room temperature (8 to 77 degrees F, 20 to 25 degrees C).